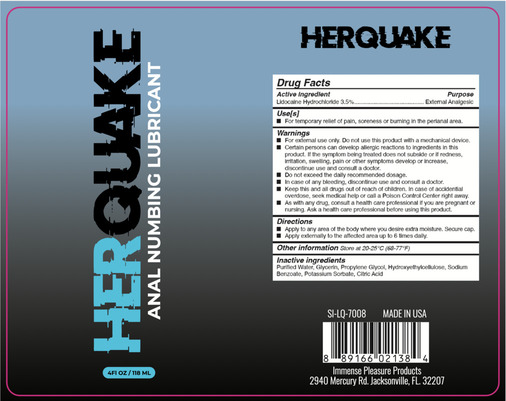 DRUG LABEL: Sunset Novelties Herquake
NDC: 77632-121 | Form: LIQUID
Manufacturer: Private Label Productions LLC
Category: otc | Type: HUMAN OTC DRUG LABEL
Date: 20250206

ACTIVE INGREDIENTS: LIDOCAINE HYDROCHLORIDE 3.5 mg/100 mL
INACTIVE INGREDIENTS: ANHYDROUS CITRIC ACID; POTASSIUM SORBATE; SODIUM BENZOATE; HYDROXYETHYLCELLULOSE; PROPYLENE GLYCOL; WATER; GLYCERIN

PLP-Sunset Novelties 118 mL Lubricant

Active Ingredient(s)

Lidocaine HCI 3.5%

Purpose

External Analgesic

Use

For temporary relief of pain, soreness or burning in the perianal area.

Warnings

For external use only. Do not use this product with a mechanical device.

Certain persons can develop allergic reactions to ingredients in this product. If the symptom being treated does not subside or if redness, irritation, swelling, pain or other symptoms develop or increase, discontinue use and consult a doctor.

Do not exceed the daily recommended dosage.

In case of any bleeding, discontinue use and consult a doctor.

Keep this and all drugs out of reach of children. In case of accidential overdose, seek medical help or call a Poison Control Center right away.

As with any drug, consult a health care professional if you are pregnant or nursing. Ask a health care professional before using this product.

Keep out of reach of childeren.

Directions

Apply to any area of the body where you desire extra moisture. Secure cap.

Apply externally to the affected area up to 6 times

Other information

Store at 20-25°C (68-77°F)

Inactive ingredients

Purified Water, Glycerin, Propylene Glycol, Hydroxyethylcellulose, Sodium Benzoate, Potassium Sorbate, Citric Acid

Package Label - Principal Display Panel

118 mL NDC:77632-121-11